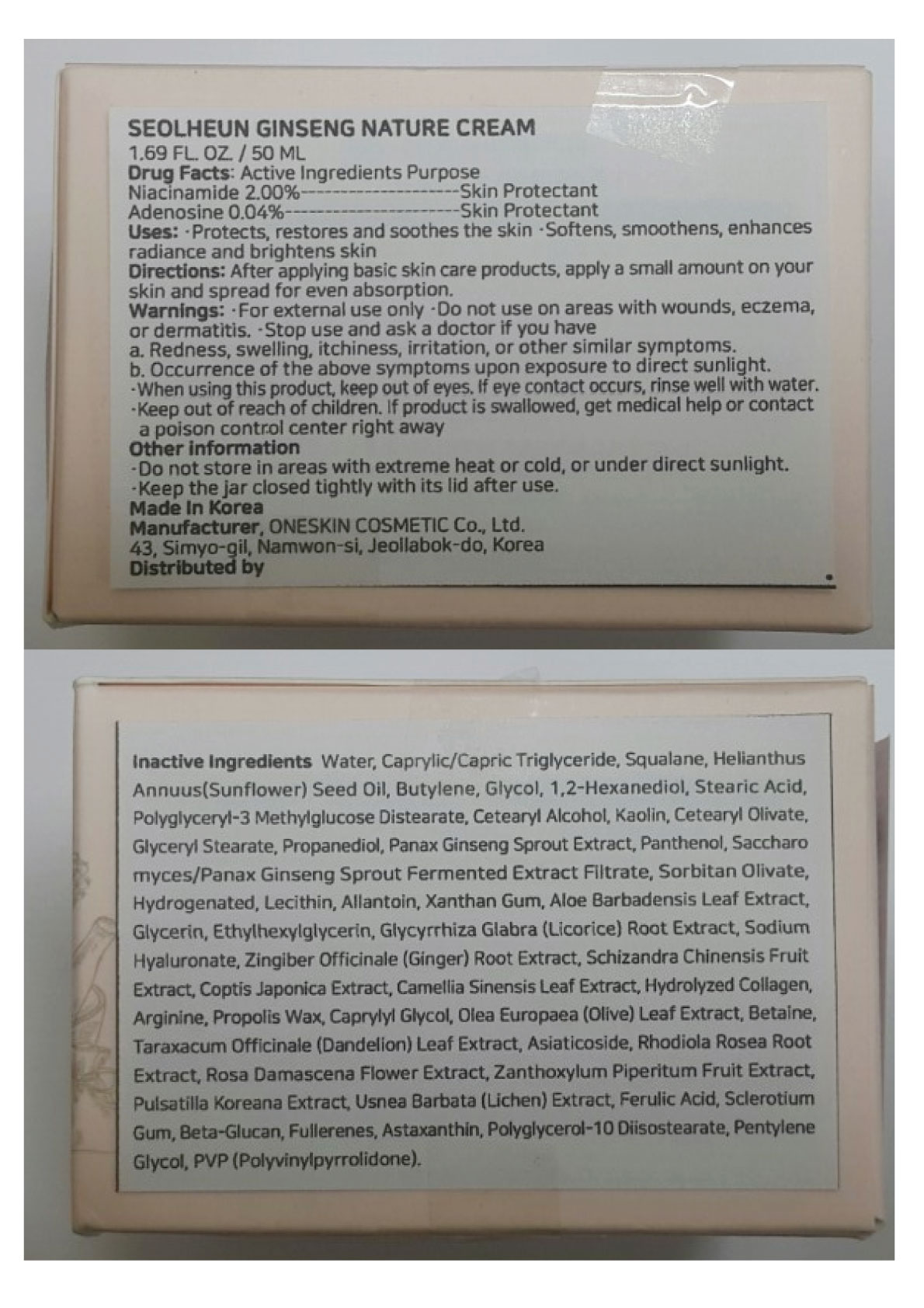 DRUG LABEL: Seolheun Ginseng Nature Cream
NDC: 70889-300 | Form: CREAM
Manufacturer: Oneskin Cosmetics Co., Ltd.
Category: otc | Type: HUMAN OTC DRUG LABEL
Date: 20200317

ACTIVE INGREDIENTS: ADENOSINE 0.02 g/50 mL; NIACINAMIDE 1 g/50 mL
INACTIVE INGREDIENTS: WATER; BUTYLENE GLYCOL; ROBINIA PSEUDOACACIA FLOWER; GLYCERIN; ASIAN GINSENG; BETAINE; ARGININE; ALLANTOIN; GLYCYRRHIZA GLABRA; GINGER; SCHISANDRA CHINENSIS FRUIT; COPTIS JAPONICA WHOLE; GREEN TEA LEAF; EDETATE DISODIUM; HYALURONATE SODIUM; GLUCONOLACTONE; PROPOLIS WAX; CAPRYLYL GLYCOL; HYACINTHUS ORIENTALIS WHOLE; JASMINUM SAMBAC FLOWER; NELUMBO NUCIFERA FLOWER; SAMBUCUS NIGRA FLOWER; PRUNUS MUME FLOWER

ACTIVE INGREDIENT

Niacinamide 2.00%

Adenosine 0.04%

PURPOSE

Skin Protectant

INDICATIONS AND USAGE

- Protects, restores and soothes the skin
- Softens, smoothens, enhances radiance and brightens skin

DOSAGE AND ADMINISTRATION

After applying basic skin care products, apply a small amount on your skin and spread for even absorption.

WARNINGS

For external use only

- Do not use on areas with wounds, eczema, or dermatitis.
- Stop use and ask a doctor if you have

a. Redness, swelling, itchiness, irritation, or other similar symptoms.
b. Occurrence of the above symptoms upon exposure to direct sunlight.

- When using this product, keep out of eyes. If eye contact occurs, rinse well with water.
- Keep out of reach of children. If product is swallowed, get medical help or contact a poison control center right away

Keep out of reach of children. If product is swallowed, get medical help or contact a poison control center right away

INACTIVE INGREDIENT

Water, Caprylic/Capric Triglyceride, Squalane, Helianthus Annuus (Sunflower) Seed Oil, Butylene Glycol, 1,2-Hexanediol, Stearic Acid, Polyglyceryl-3 Methylglucose Distearate, Cetearyl Alcohol, Kaolin, Cetearyl Olivate, Glyceryl Stearate, Propanediol, Panax Ginseng Sprout Extract, Panthenol, Saccharomyces/Panax Ginseng Sprout Fermented Extract Filtrate, Sorbitan Olivate, Hydrogenated Lecithin, Allantoin, Xanthan Gum, Aloe Barbadensis Leaf Extract, Glycerin, Ethylhexylglycerin, Glycyrrhiza Glabra (Licorice) Root Extract, Sodium Hyaluronate, Zingiber Officinale (Ginger) Root Extract, Schizandra Chinensis Fruit Extract, Coptis Japonica Extract, Camellia Sinensis Leaf Extract, Hydrolyzed Collagen, Arginine, Propolis Wax, Caprylyl Glycol, Olea Europaea (Olive) Leaf Extract, Betaine, Taraxacum Officinale (Dandelion) Leaf Extract, Asiaticoside, Rhodiola Rosea Root Extract, Rosa Damascena Flower Extract, Zanthoxylum Piperitum Fruit Extract, Pulsatilla Koreana Extract, Usnea Barbata (Lichen) Extract, Ferulic Acid, Sclerotium Gum, Beta-Glucan, Fullerenes, Astaxanthin, Polyglycerol-10 Diisostearate, Pentylene Glycol, PVP (Polyvinylpyrrolidone).

OTHER SAFETY INFORMATION

- Do not store in areas with extreme heat or cold, or under direct sunlight.
- Keep the jar closed tightly with its lid after use.

PACKAGE LABEL

SEOLHEUN GINSENG NATURE CREAM